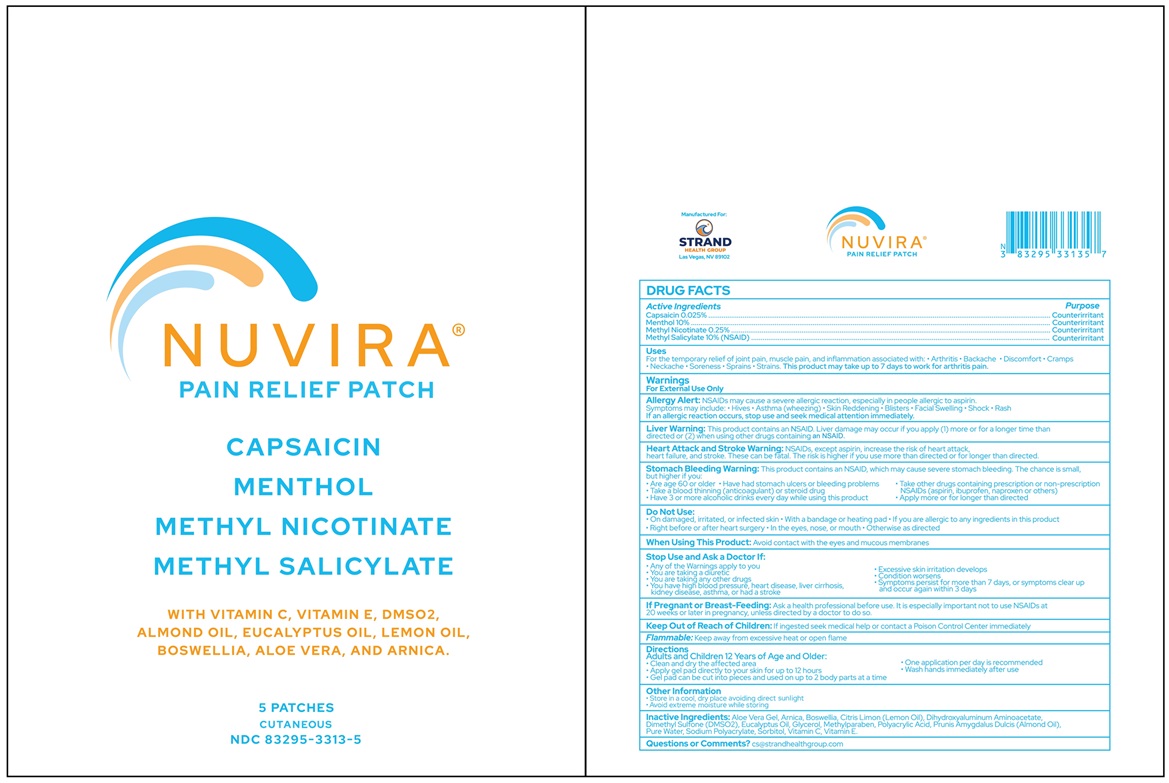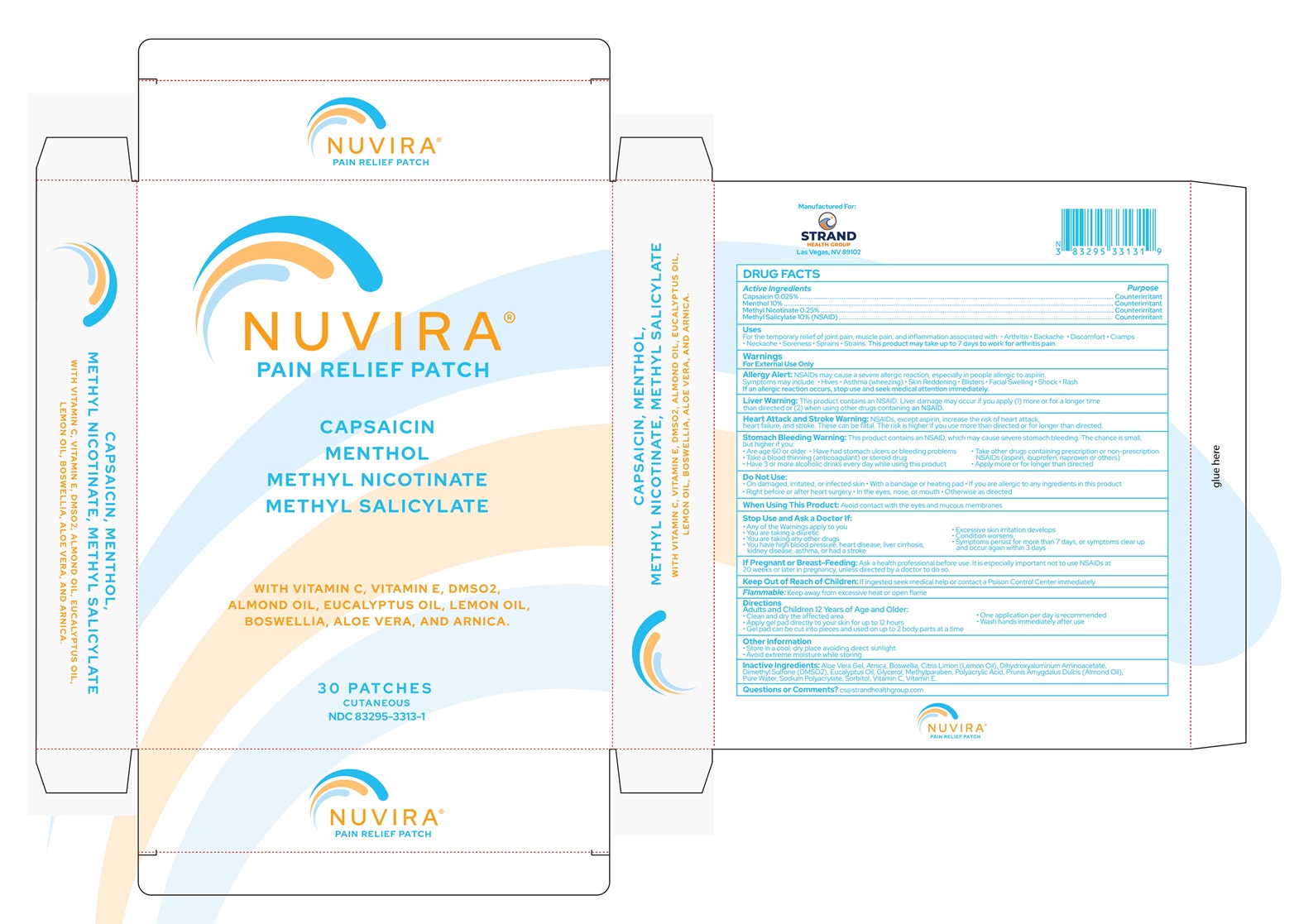 DRUG LABEL: Nuvira
NDC: 83295-3313 | Form: PATCH
Manufacturer: Strand Health Group
Category: otc | Type: HUMAN OTC DRUG LABEL
Date: 20240816

ACTIVE INGREDIENTS: METHYL NICOTINATE 0.0025 g/1 g; METHYL SALICYLATE 0.1 g/1 g; CAPSAICIN 0.00025 g/1 g; MENTHOL 0.1 g/1 g
INACTIVE INGREDIENTS: SODIUM POLYACRYLATE (2500000 MW); WATER; SORBITOL; DIMETHYL SULFONE; METHYLPARABEN; EUCALYPTUS OIL; GLYCERIN; ARNICA MONTANA FLOWER; POLYACRYLIC ACID (250000 MW); ASCORBIC ACID; ALPHA-TOCOPHEROL; DIHYDROXYALUMINUM AMINOACETATE; ALOE VERA LEAF; FRANKINCENSE; LEMON OIL, DISTILLED; ALMOND OIL

Nuvira Patch

Active Ingredients

Capsaicin 0.025%

Menthol 10%

Methyl Nicotinate 0.25%

Methyl Salicylate 10% (NSAID)

Purpose

Counterirritant

Counterirritant

Counterirritant

Counterirritant

Uses

For the temporary relief of joint pain, muscle pain, and inflammation associated with:

- Arthritis
- Backache
- Discomfort
- Cramps
- Neckache
- Soreness
- Sprains
- Strains

This product may take up to 7 days to work for arthritis pain.

Warnings

For External Use Only Topical use only

Allergy Alert: NSAIDs may cause a severe allergic reaction, especially in people allergic to aspirin. Symptoms may include:

- Hives
- Asthma (wheezing)
- Skin Reddening
- Blisters
- Facial Swelling
- Shock
- Rash

If an allergic reaction occurs, stop use and seek medical attention immediately.

Liver Warning: This product contains an NSAID. Liver damage may occur if you apply (1) more or for a longer time than directed or (2) when using other drugs containing an NSAID.

Stomach Bleeding Warning: This product contains an NSAID, which may cause severe stomach bleeding. The chance is small, but higher if you:

- Are age 60 or older
- Have had stomach ulcers or bleeding problems
- Take a blood thinning (anticoagulant) or steroid drug
- Take other drugs containing prescription or non-prescription NSAIDs (aspirin, ibuprofen, naproxen or others)
- Have 3 or more alcoholic drinks every day while using this product
- Apply more or for longer than directed

Heart Attack and Stroke Warning: NSAIDs, except aspirin, increase the risk of heart attack, heart failure, and stroke. These can be fatal. The risk is higher if you use more than directed or for longer than directed.

Do Not Use

- On damaged, irritated, or infected skin
- With a bandage or heating pad
- If you are allergic to any ingredients in this product
- Right before or after heart surgery
- In the eyes, nose, or mouth
- Otherwise as directed

When Using This Product

Avoid contact with the eyes and mucous membranes

Stop Use and Ask a Doctor If

- Any of the Warnings apply to you
- You are taking a diuretic
- You are taking any other drugs
- You have high blood pressure, heart disease, liver cirrhosis, kidney disease, asthma, or had a stroke
- Excessive skin irritation develops
- Condition worsens
- Symptoms persist for more than 7 days, or symptoms clear up and occur again within 3 days

If Pregnant or Breast-Feeding

Ask a health professional before use. It is especially important not to use NSAIDs at 20 weeks or later in pregnancy, unless directed by a doctor to do so.

Keep Out of Reach of Children

If ingested seek medical help or contact a Poison Control Center immediately

Flammable

Keep away from excessive heat or open flame

Directions

Adults and Children 12 Years of Age and Older:

- Clean and dry the affected area
- Apply gel pad directly to your skin for up to 12 hours
- Gel pad can be cut into pieces and used on up to 2 body parts at a time
- One application per day is recommended
- Wash hands immediately after use

Other Information

- Store in a cool, dry place with lid tightly closed.
- If the tamper-evident foil seal is not intact, do not use

Inactive Ingredients

Aloe Vera Gel, Arnica, Boswellia, Citris Limon (Lemon Oil), Dihydroxyaluminum Aminoacetate, Dimethyl Sulfone (DMSO2), Eucalyptus Oil, Glycerol, Methylparaben, Polyacrylic Acid, Prunis Amygdalus Dulcis (Almond Oil), Pure Water, Sodium Polyacrylate, Sorbitol, Vitamin C, Vitamin E.

Questions or Comments?

cs@strandhealthgroup.com